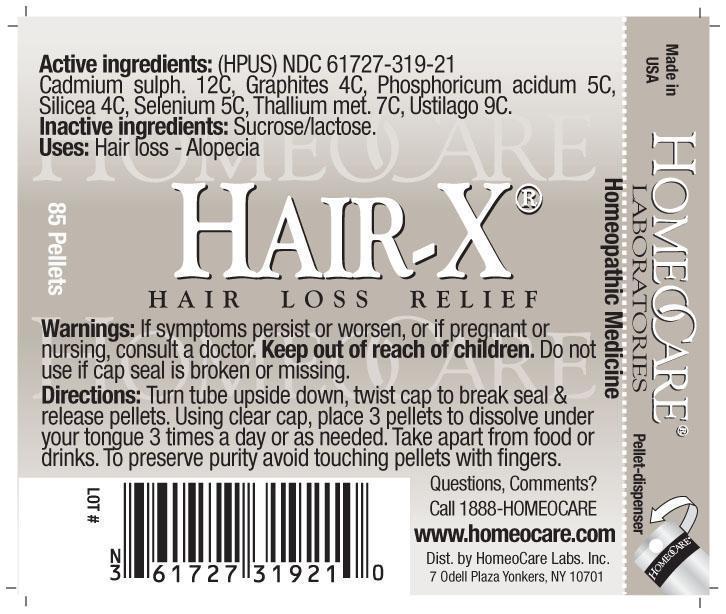 DRUG LABEL: Hair-X Hair Loss Relief
NDC: 61727-319 | Form: PELLET
Manufacturer: Homeocare Laboratories
Category: homeopathic | Type: HUMAN OTC DRUG LABEL
Date: 20181231

ACTIVE INGREDIENTS: CADMIUM SULFATE 12 [hp_C]/4 g; GRAPHITE 4 [hp_C]/4 g; PHOSPHORIC ACID 5 [hp_C]/4 g; SILICON DIOXIDE 4 [hp_C]/4 g; SELENIUM 5 [hp_C]/4 g; THALLIUM 7 [hp_C]/4 g; USTILAGO MAYDIS 9 [hp_C]/4 g
INACTIVE INGREDIENTS: SUCROSE; LACTOSE

Hair-X Hair Loss Relief

Active Ingredients:

Cadmium sulph. 12C, Graphites 4C, Phosphoricum acidum 5C, Silicea 4C, Selenium 5C, Thallium met. 7C, Ustilago 9C.

Inactive Ingredients:

Sucrose/lactose.

Keep out of reach of children.

Purpose:

Hair loss-Alopecia.

Indications & Usage:

Turn tube upside down, twist cap to break seal & release pellets. Using clear cap, place 3 pellets to dissolve under your tongue 3 times a day or as needed. Take apart from food or drinks. To preserve purity avoid touching pellets with fingers.

Dosage & Administration:

Turn tube upside down, twist cap to break seal & release pellets. Using clear cap, place 3 pellets to dissolve under your tongue 3 times a day or as needed. Take apart from food or drinks. To preserve purity avoid touching pellets with fingers.

Warnings:

If symptoms persist or worsen, or if pregnant or nursing, consult a doctor. Keep out of reach of children. Do not use if cap seal is broken or missing.

Hair-X Hair Loss Relief

Homeopathic Medicine

85 Pellets
hcl_label_hairx 2012.jpg